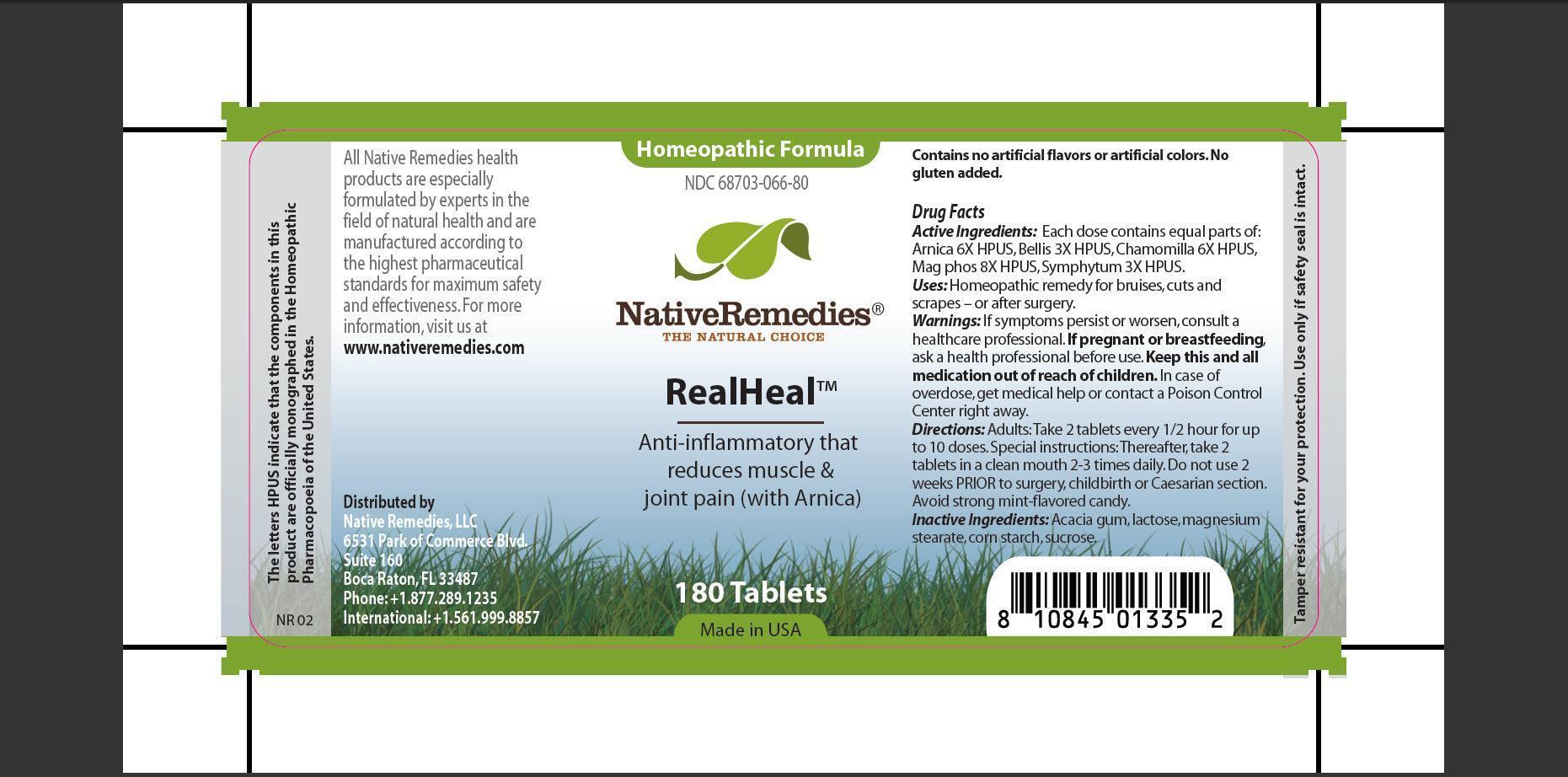 DRUG LABEL: RealHeal
NDC: 68703-066 | Form: TABLET
Manufacturer: Native Remedies, LLC
Category: homeopathic | Type: HUMAN OTC DRUG LABEL
Date: 20130121

ACTIVE INGREDIENTS: ARNICA MONTANA 3 [hp_X]/1 1; BELLIS PERENNIS 3 [hp_X]/1 1; MATRICARIA RECUTITA 6 [hp_X]/1 1; MAGNESIUM PHOSPHATE, DIBASIC TRIHYDRATE 8 [hp_X]/1 1; COMFREY ROOT 3 [hp_X]/1 1
INACTIVE INGREDIENTS: ACACIA; LACTOSE; MAGNESIUM STEARATE; STARCH, CORN; SUCROSE

RealHeal

PURPOSE

Anti-inflammatory that reduces muscle and joint pain (with Arnica)

ACTIVE INGREDIENT

Active Ingredients: Each dose contains equal parts of: Arnica 6X HPUS, Bellis 3X HPUS, Chamomilla 6X HPUS, Mag phos 8X HPUS, Symphytum 3X HPUS.

INDICATIONS AND USAGE

Uses: Homeopathic remedy for bruises, cuts and scrapes - or after surgery.

WARNINGS

Warnings: If symptoms persist or worsen, consult a healthcare professional.

PREGNANCY OR BREAST FEEDING

If pregnant or breastfeeding, ask healthcare professional before use.

KEEP OUT OF REACH OF CHILDREN

Keep this and all medication out of reach of children.

OVERDOSAGE

In case of overdose, get medical help or contact a Poison Control Center right away.

DOSAGE AND ADMINISTRATION

Directions: Adults: Take 2 tablets every 1/2 hour for up to 10 doses. Special instructions: Thereafter, take 2 tablets in a clean mouth 2-3 times daily. Do not use 2 weeks PRIOR to surgery, childbirth or Caesarian section. Avoid strong mint-flavored candy.

INACTIVE INGREDIENT

Inactive Ingredients: Acacia gum, lactose, magnesium stearate, corn starch, sucrose.

PATIENT COUNSELING INFORMATION

The letters HPUS indicate that the components in this product are officially monographed in the Homeopathic Pharmacopoeia of the United States.

All Native Remedies health products are especially formulated by experts in the field of natural health and are manufactured according to the highest pharmaceutical standards for maximum safety and effectiveness. For more information, visit us at www.nativeremedies.com

Distributed by
Native Remedies, LLC
6531 Park of Commerce Blvd,
Suite 160
Boca Raton, Fl 33487
Phone:+1.877.289.1235
International:+1.561.999.8857

Contains no artificial flavors of artificial colors. No gluten added.

STORAGE AND HANDLING

Tamper resistant for your protection. Use only if safety seal is intact.